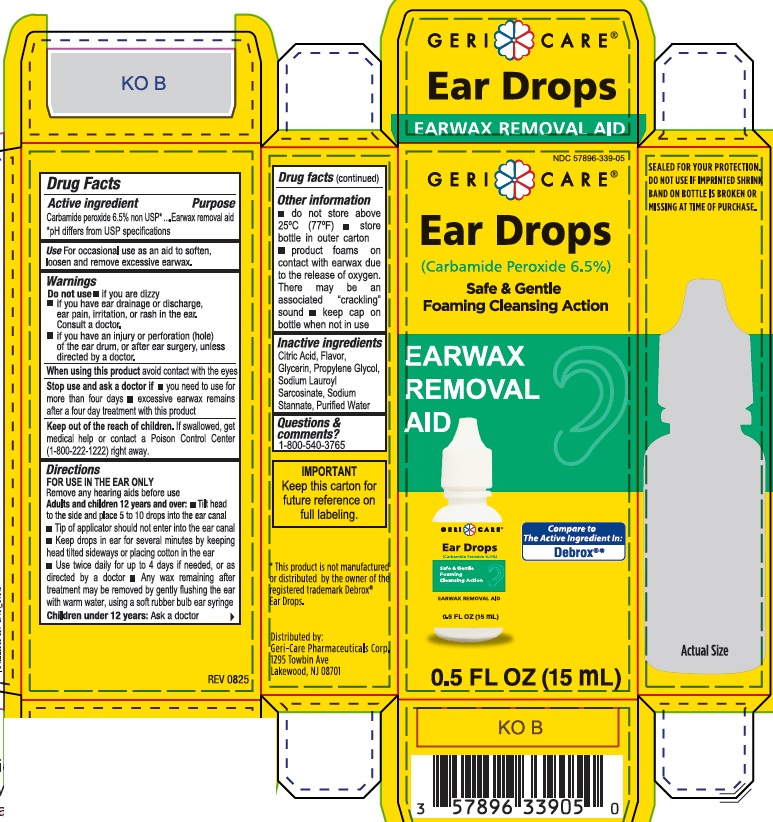 DRUG LABEL: Ear Wax Removal Drops
NDC: 57896-339 | Form: SOLUTION/ DROPS
Manufacturer: GeriCare Pharmaceutical Corp
Category: otc | Type: HUMAN OTC DRUG LABEL
Date: 20251209

ACTIVE INGREDIENTS: CARBAMIDE PEROXIDE 65 mg/1 mL
INACTIVE INGREDIENTS: GLYCERIN; ANHYDROUS CITRIC ACID; PROPYLENE GLYCOL; SODIUM LAUROYL SARCOSINATE; SODIUM STANNATE; WATER

Drug Facts

Active ingredient

Carbamide Peroxide 6.5% non USP*

*pH differs from USP specifications

PURPOSE

Earwax removal aid

Uses

For occasional use as an aid to soften, loosen and remove excessive ear wax.

Warnings

Do not use

- if you are dizzy
- if you have ear drainage or discharge, ear pain, irritation or rashin the ear. Consult your doctor.
- if you have an injury or perforation (hole) of the ear drum or after ear surgery, unless directed by a doctor

When using this product

avoid contact with the eyes.

Stop use and ask a doctor if

- you need to use for more than four days
- excessive earwax remains after a four day treatment with this product

Keep out of the reach of children

If swallowed, get medical help or contact a Poison Control Center (1-800-222-1222) right away.

Directions

FOR USE IN THE EAR ONLY

Remove any hearing aids before use

Adults and children over 12 years and over:

- Tilt head to the side and place 5 to 10 drops into the ear canal
- Tip of applicator should not enter ear canal.
- Keep drops in ear for several minutes by keeping head tilted or placing cotton in the ear.
- Use twice daily for up to 4 days if needed, or as directed by a doctor.
- Any earwax remaining after treatment may be removed by gently flushing the ear with warm water, using a soft rubber bulb ear syringe.

Children under 12 years: Ask a doctor.

Other information

- do not store above 25C (77F)
- store bottle in outer carton
- product foams on contact with earwax due to the release of oxygen. There may be an associated "crackling" sound
- Keep cap on bottle when not in use

Inactive ingredients

Citric Acid, Flavor, Glycerin, Propylene Glycol, Sodium Lauroyl Sarcosinate, Sodium Stannate, Purified Water

Questions & comments?

1-800-540-3765